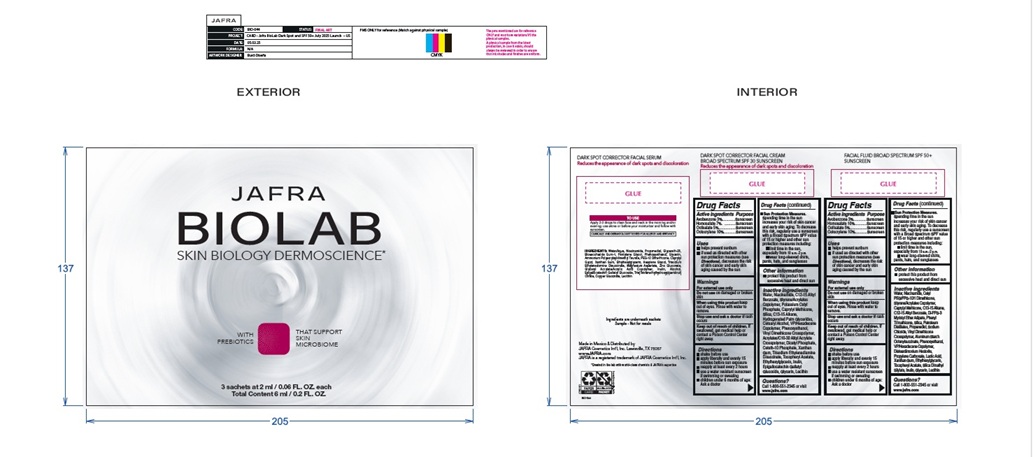 DRUG LABEL: JAFRA BIOLAB SUNSCREENS AND CLEANSER
NDC: 68828-603 | Form: KIT | Route: TOPICAL
Manufacturer: Distribuidora Comercial Jafra, S.A. de C.V.
Category: otc | Type: HUMAN OTC DRUG LABEL
Date: 20250520

ACTIVE INGREDIENTS: AVOBENZONE 3 g/100 mL; HOMOSALATE 7 g/100 mL; OCTISALATE 5 g/100 mL; OCTOCRYLENE 10 g/100 mL; AVOBENZONE 3 g/100 mL; HOMOSALATE 10 g/100 mL; OCTISALATE 5 g/100 mL; OCTOCRYLENE 10 g/100 mL
INACTIVE INGREDIENTS: ETHYLHEXYLGLYCERIN; GLYCERIN; SILICON DIOXIDE; PHENOXYETHANOL; .ALPHA.-TOCOPHEROL ACETATE; WATER; NIACINAMIDE; CAPRYLYL TRISILOXANE; C13-15 ALKANE; ALKYL (C12-15) BENZOATE; DIMETHICONE/VINYL DIMETHICONE CROSSPOLYMER (SOFT PARTICLE); VINYLPYRROLIDONE/HEXADECENE COPOLYMER; XANTHAN GUM; INULIN; SOYBEAN LECITHIN; POTASSIUM CETYL PHOSPHATE; HYDROGENATED PALM GLYCERIDES; CETOSTEARYL ALCOHOL; CARBOMER COPOLYMER TYPE B (ALLYL PENTAERYTHRITOL CROSSLINKED); DIHEXADECYL PHOSPHATE; CETETH-10 PHOSPHATE; TRISODIUM ETHYLENEDIAMINE DISUCCINATE; EPIGALLOCATECHIN GALLATYL GLUCOSIDE; ETHYLHEXYLGLYCERIN; GLYCERIN; SILICON DIOXIDE; PHENOXYETHANOL; .ALPHA.-TOCOPHEROL ACETATE; WATER; NIACINAMIDE; CETYL PEG/PPG-10/1 DIMETHICONE (HLB 5); CAPRYLYL TRISILOXANE; C13-15 ALKANE; ALKYL (C12-15) BENZOATE; DI-PPG-3 MYRISTYL ETHER ADIPATE; PHENYL TRIMETHICONE; PROPANEDIOL; SODIUM CHLORIDE; DIMETHICONE/VINYL DIMETHICONE CROSSPOLYMER (SOFT PARTICLE); ALUMINUM STARCH OCTENYLSUCCINATE; VINYLPYRROLIDONE/HEXADECENE COPOLYMER; DISTEARDIMONIUM HECTORITE; PROPYLENE CARBONATE; LACTIC ACID, UNSPECIFIED FORM; XANTHAN GUM; SILICA DIMETHYL SILYLATE; INULIN; SOYBEAN LECITHIN

JAFRA BIOLAB SUNSCREENS AND CLEANSER KIT

Active ingredient(s)

Part 2: JAFRA BIOLAB DARK SPOT CORRECTOR FACIAL CREAM BROAD SPECTRUM SPF 30 SUNSCREEN

Avobenzone 3%
Homosalate 7%
Octisalate 5%
Octocrylene 10%

Part 3: JAFRA BIOLAB FACIAL FLUID BROAD SPECTRUM SPF 50+ SUNSCREEN
Avobenzone 3%
Homosalate 10%
Octisalate 5%
Octocrylene 10%

Purpose

Sunscreen

Uses

• helps prevent sunburn

• if used as directed with other sun protection measures (see Directions), decreases the risk of skin cancer and early skin aging

caused by the sun

Warnings

For external use only

Do not useon damaged or broken skin

When using this productkeep out of eyes. Rinse with water to remove.

Stop use and ask a doctor ifrash occurs

Keep out of reach of children. If swallowed, get medical help or contact a Poison Control Center right away.

Directions

• shake before use

• apply liberally and evenly 15 minutes before sun exposure

• reapply at least every 2 hours

• use a water resistant sunscreen if swimming or sweating

• children under 6 months of age: Ask a doctor

• Sun Protection Measures. Spending time in the sun increases your risk of skin cancer and early skin aging.

To decrease this risk, regularly use a sunscreen with a Broad Spectrum SPF value of 15 or higher and other sun protection measures including:
• limit time in the sun, especially from 10 a.m. – 2 p.m.
• wear long-sleeved shirts, pants, hats, and sunglasses

Other information

• protect this product from excessive heat and direct sun

Inactive ingredients

Part 2: JAFRA BIOLAB DARK SPOT CORRECTOR FACIAL CREAM BROAD SPECTRUM SPF 30 SUNSCREEN
Water, Niacinamide, C12-15 Alkyl Benzoate, Styrene/Acrylates Copolymer, Potassium Cetyl Phosphate, Caprylyl Methicone, Silica, C13-15 Alkane, Hydrogenated Palm Glycerides, Cetearyl Alcohol, VP/Hexadecene Copolymer, Phenoxyethanol, Vinyl Dimethicone Crosspolymer, Acrylates/C10-30 Alkyl Acrylate Crosspolymer, Dicetyl Phosphate, Ceteth-10 Phosphate, Xanthan Gum, Trisodium Ethylenediamine Disuccinate, Tocopheryl Acetate, Ethylhexylglycerin, Inulin, Epigallocatechin Gallatyl Glucoside, Glycerin, Lecithin

Part 3: JAFRA BIOLAB FACIAL FLUID BROAD SPECTRUM SPF 50+ SUNSCREEN
Water, Niacinamide, Cetyl PEG/PPG-10/1 Dimethicone, Styrene/Acrylates Copolymer, Caprylyl Methicone, C13-15 Alkane, C12-15 Alkyl Benzoate, Di-PPG-3 Myristyl Ether Adipate, Phenyl Trimethicone, Silica, Petroleum Distillates, Propanediol, Sodium Chloride, Vinyl Dimethicone Crosspolymer, Aluminum Starch Octenylsuccinate, Phenoxyethanol, VP/Hexadecene Copolymer, Disteardimonium Hectorite, Propylene Carbonate, Lactic Acid, Xanthan Gum, Ethylhexylglycerin, Tocopheryl Acetate, Silica Dimethyl Silylate, Inulin, Glycerin, Lecithin

Questions?
Call 1-800-551-2345 or visit www.jafra.com